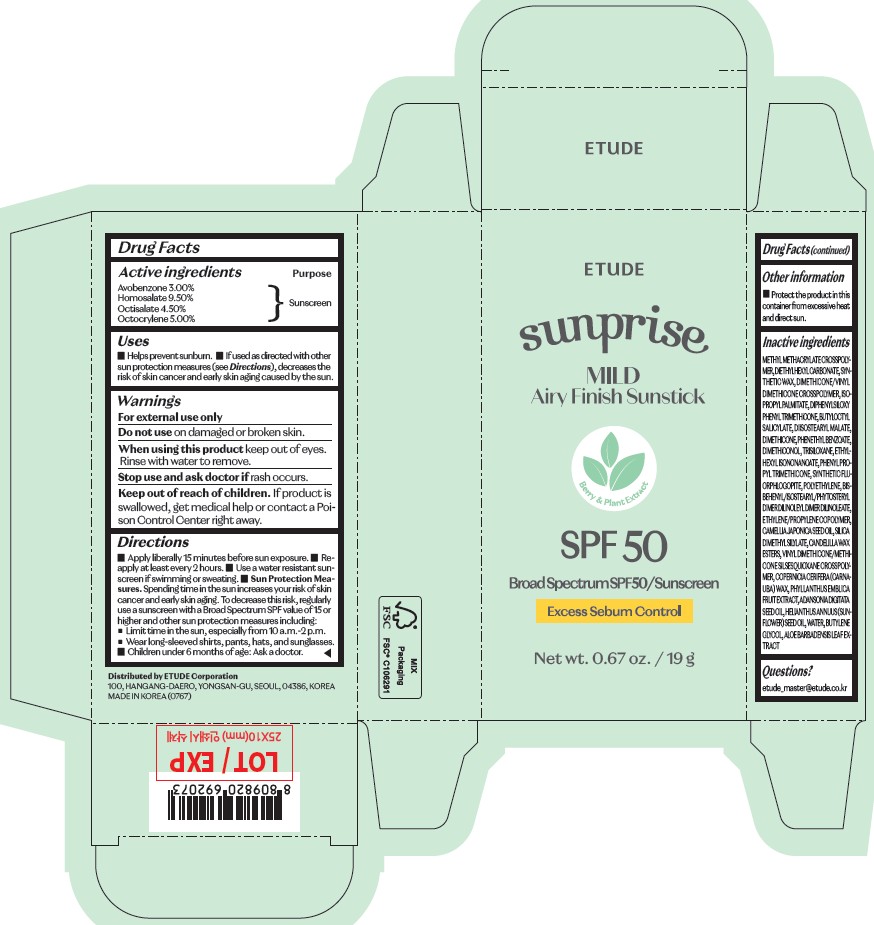 DRUG LABEL: ETUDE SunPrise Mild Airy Finish Sunstick
NDC: 84468-743 | Form: STICK
Manufacturer: ETUDE CORPORATION
Category: otc | Type: HUMAN OTC DRUG LABEL
Date: 20250217

ACTIVE INGREDIENTS: OCTISALATE 4.5 g/100 g; OCTOCRYLENE 5 g/100 g; AVOBENZONE 3 g/100 g; HOMOSALATE 9.5 g/100 g
INACTIVE INGREDIENTS: DIETHYLHEXYL CARBONATE; ISOPROPYL PALMITATE

Route of administration

TOPICAL

Warnings

- For external use only
- Do not use on damaged or broken skin.
- When using this product keep out of eyes. Rinse with water to remove.
- Stop use and ask doctor if rash occurs.
- Keep out of reach of children. If product is swallowed, get medical help or contact a Poison Control Center right away.

Inactive ingredients

METHYL METHACRYLATE CROSSPOLYMER, DIETHYLHEXYL CARBONATE, SYNTHETIC WAX, DIMETHICONE/VINYL DIMETHICONE CROSSPOLYMER, ISOPROPYL PALMITATE, DIPHENYLSILOXY PHENYL TRIMETHICONE, BUTYLOCTYL SALICYLATE, DIISOSTEARYL MALATE, DIMETHICONE, PHENETHYL BENZOATE, DIMETHICONOL, TRISILOXANE, ETHYLHEXYL ISONONANOATE, PHENYL PROPYL TRIMETHICONE, SYNTHETIC FLUORPHLOGOPITE, POLYETHYLENE, BIS-BEHENYL/ISOSTEARYL/PHYTOSTERYL DIMER DILINOLEYL DIMER DILINOLEATE, ETHYLENE/PROPYLENE COPOLYMER, CAMELLIA JAPONICA SEED OIL, SILICA DIMETHYL SILYLATE, CANDELILLA WAX ESTERS, VINYL DIMETHICONE/METHICONE SILSESQUIOXANE CROSSPOLYMER, COPERNICIA CERIFERA (CARNAUBA) WAX, PHYLLANTHUS EMBLICA FRUIT EXTRACT, ADANSONIA DIGITATA SEED OIL, HELIANTHUS ANNUUS (SUNFLOWER) SEED OIL, WATER, BUTYLENE GLYCOL, ALOE BARBADENSIS LEAF EXTRACT

Uses

◼ Helps prevent sunburn. ◼ If used as directed with other sun protection measures (see Directions), decreases the risk of skin cancer and early skin aging caused by the sun.

Keep out of reach of children.

If product is swallowed, get medical help or contact a Poison Control Center right away.

Purpose

Sunscreen